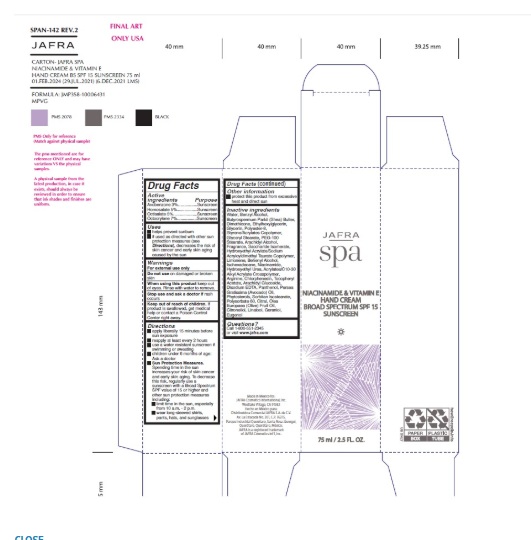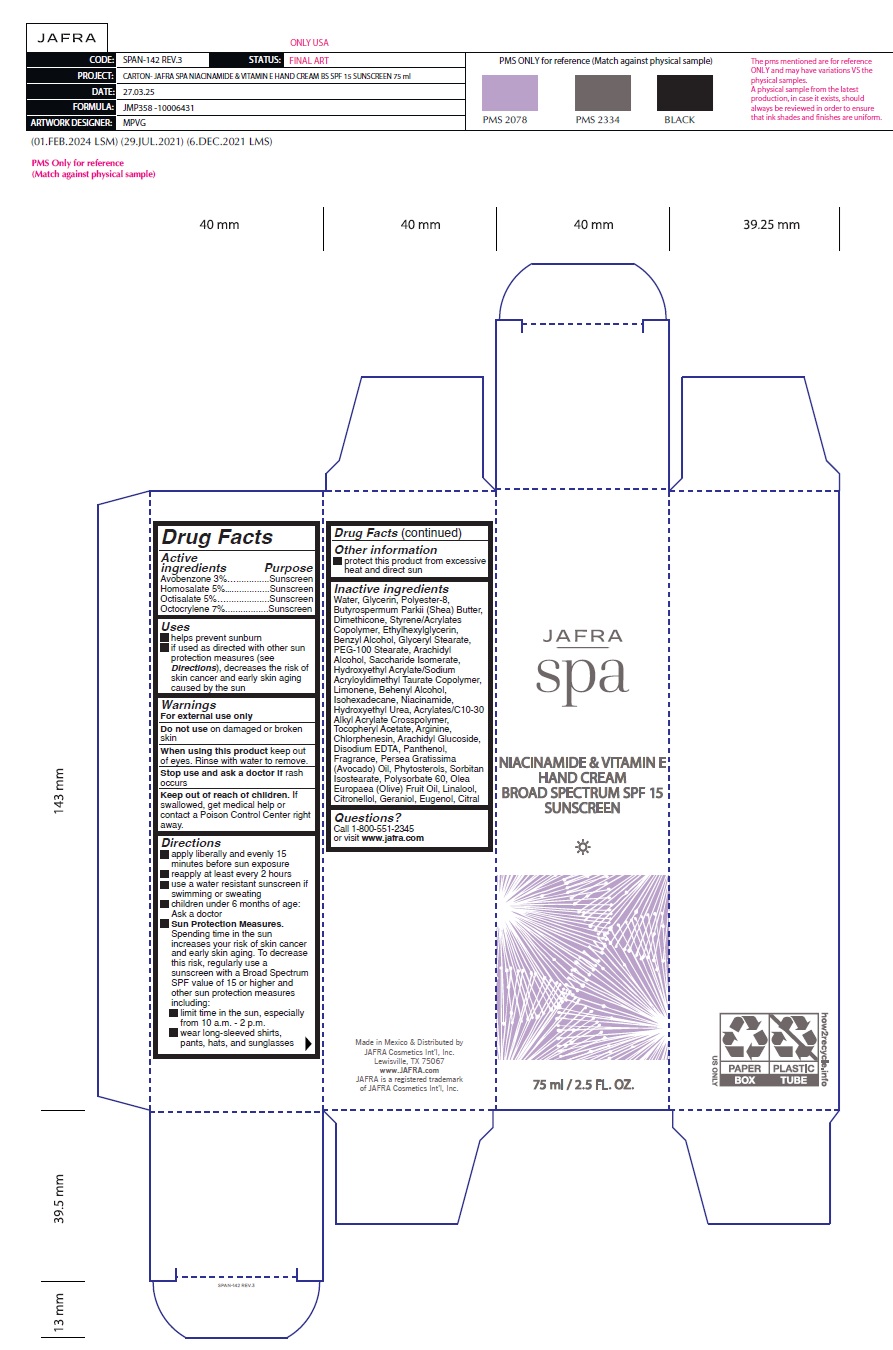 DRUG LABEL: Spa Niacinamide And Vitamin E Hand Cream Broad Spectrum SPF 15
NDC: 68828-003 | Form: CREAM
Manufacturer: Distribuidora Comercial Jafra, S.A. de C.V.
Category: otc | Type: HUMAN OTC DRUG LABEL
Date: 20251105

ACTIVE INGREDIENTS: AVOBENZONE 3 g/100 mL; HOMOSALATE 5 g/100 mL; OCTISALATE 5 g/100 mL; OCTOCRYLENE 7 g/100 mL
INACTIVE INGREDIENTS: WATER; GLYCERIN; SHEA BUTTER; DIMETHICONE; ETHYLHEXYLGLYCERIN; BENZYL ALCOHOL; GLYCERYL MONOSTEARATE; PEG-100 STEARATE; ARACHIDYL ALCOHOL; SACCHARIDE ISOMERATE; HYDROXYETHYL ACRYLATE/SODIUM ACRYLOYLDIMETHYL TAURATE COPOLYMER (100000 MPA.S AT 1.5%); DOCOSANOL; ISOHEXADECANE; NIACINAMIDE; HYDROXYETHYL UREA; CARBOMER COPOLYMER TYPE B (ALLYL PENTAERYTHRITOL CROSSLINKED); .ALPHA.-TOCOPHEROL ACETATE; ARGININE; CHLORPHENESIN; ARACHIDYL GLUCOSIDE; EDETATE DISODIUM; PANTHENOL; AVOCADO OIL; SORBITAN ISOSTEARATE; POLYSORBATE 60; OLIVE OIL; POLYESTER-8 (1400 MW, CYANODIPHENYLPROPENOYL CAPPED); LIMONENE, (+)-; .BETA.-CITRONELLOL, (+/-)-; LINALOOL, (+/-)-; GERANIOL; EUGENOL; CITRAL

Active ingredients

Avobenzone 3%
Homosalate 5%
Octisalate 5%
Octocrylene 7%

Purpose

Sunscreen

Uses

- Helps prevent sunburn

- If used as directed with other sun protection measures (see Directions), decreases the risk of skin cancer and early skin aging caused by the sun.

Warnings

For external use only
Do not use on damaged or broken skin
When using this product keep out of eyes. Rinse with water to remove.
Stop use and ask a doctor if rash occurs
Keep out of reach of children. If swallowed, get medical help or contact a Poison Control Center right away.

Directions

• Apply liberally and evenly 15 minutes before sun exposure
• Reapply at least every 2 hours
• Use a water resistant sunscreen if swimming or sweating
• Children under 6 months of age: Ask a doctor
• Sun Protection Measures.Spending time in the sun increases your risk of skin cancer and early skin aging. To decrease this risk, regularly use a sunscreen with a Broad Spectrum SPF value of 15 or higher and other sun protection measures including:
• limit your time in the sun, especially from 10 a.m. – 2 p.m.
• wear long-sleeved shirts, pants, hats, and sunglasses

Other information

- protect this product from excessive heat and direct sun

Inactive ingredients

Water, Glycerin, Polyester-8, Butyrospermum Parkii (Shea) Butter, Dimethicone, Styrene/Acrylates Copolymer, Ethylhexylglycerin, Benzyl Alcohol, Glyceryl Stearate, PEG-100 Stearate, Arachidyl Alcohol, Saccharide Isomerate, Hydroxyethyl Acrylate/Sodium Acryloyldimethyl Taurate Copolymer, Limonene, Behenyl Alcohol, Isohexadecane, Niacinamide, Hydroxyethyl Urea, Acrylates/C10-30 Alkyl Acrylate Crosspolymer, Tocopheryl Acetate, Arginine, Chlorphenesin, Arachidyl Glucoside, Disodium EDTA, Panthenol, Fragrance, Persea Gratissima (Avocado) Oil, Phytosterols, Sorbitan Isostearate, Polysorbate 60, Olea Europaea (Olive) Fruit Oil, Linalool, Citronellol, Geraniol, Eugenol, Citral

Questions?Call 1-800-551-2345 or visit www.jafra.com